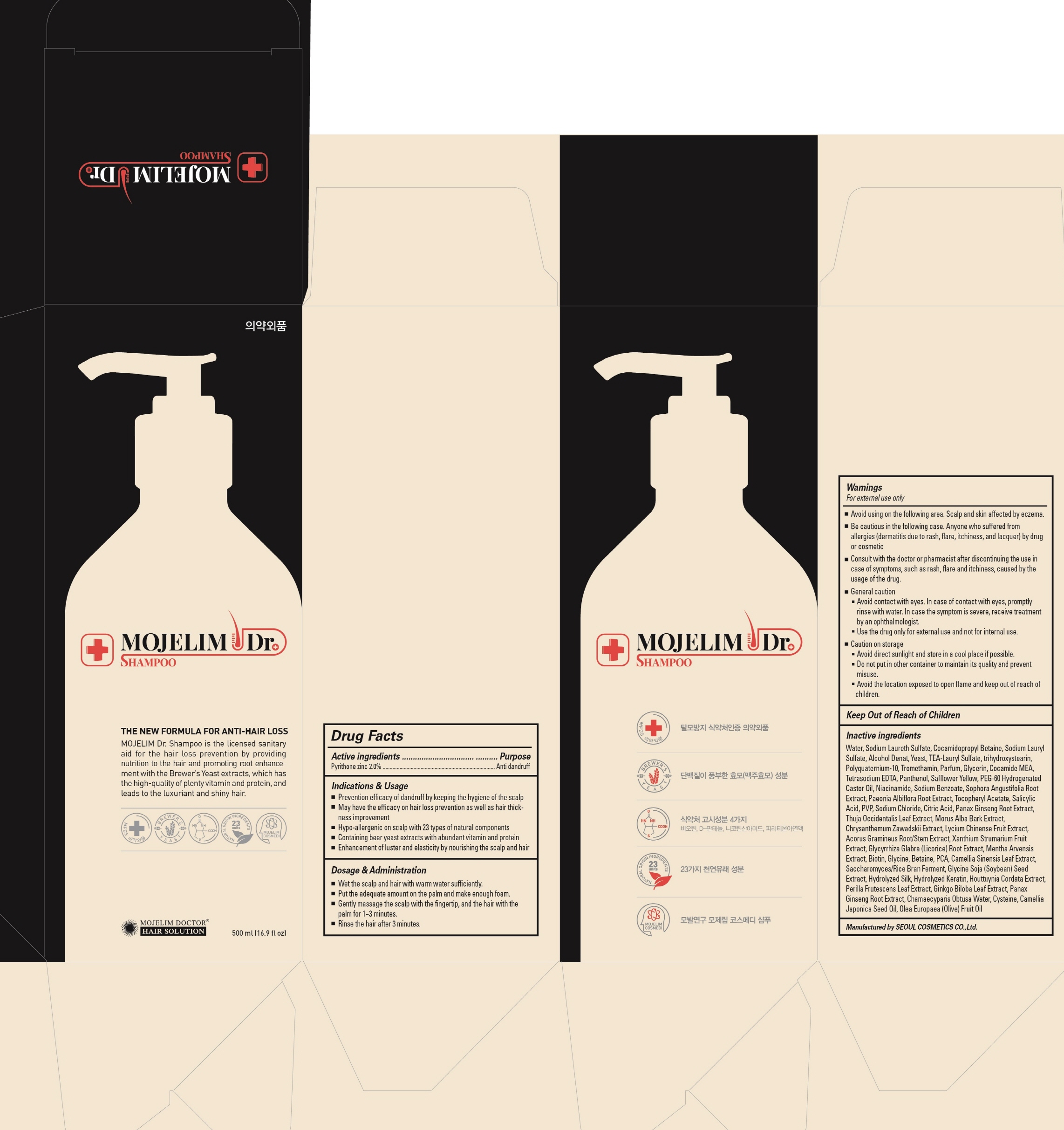 DRUG LABEL: MOJELIM Dr
NDC: 71194-010 | Form: SHAMPOO
Manufacturer: MOJELIM COSMEDI CO., LTD
Category: otc | Type: HUMAN OTC DRUG LABEL
Date: 20170227

ACTIVE INGREDIENTS: PYRITHIONE ZINC 10.0 g/500 mL
INACTIVE INGREDIENTS: Water; Sodium Laureth Sulfate

ACTIVE INGREDIENT

Active ingredients: PYRITHIONE ZINC 2.0%

INACTIVE INGREDIENT

Inactive ingredients: Water, Sodium Laureth Sulfate, Cocamidopropyl Betaine, Sodium Lauryl Sulfate, Alcohol Denat, Yeast, TEA-Lauryl Sulfate, trihydroxystearin, Polyquaternium-10, Tromethamin, Parfum, Glycerin, Cocamide MEA, Tetrasodium EDTA, Panthenol, Safflower Yellow, PEG-60 Hydrogenated Castor Oil, Niacinamide, Sodium Benzoate, Sophora Angustifolia Root Extract, Paeonia Albiflora Root Extract, Tocopheryl Acetate, Salicylic Acid, PVP, Sodium Chloride, Citric Acid, Panax Ginseng Root Extract, Thuja Occidentalis Leaf Extract, Morus Alba Bark Extract, Chrysanthemum Zawadskii Extract, Lycium Chinense Fruit Extract, Acorus Gramineus Root/Stem Extract, Xanthium Strumarium Fruit Extract, Glycyrrhiza Glabra (Licorice) Root Extract, Mentha Arvensis Extract, Biotin, Glycine, Betaine, PCA, Camellia Sinensis Leaf Extract, Saccharomyces/Rice Bran Ferment, Glycine Soja (Soybean) Seed Extract, Hydrolyzed Silk, Hydrolyzed Keratin, Houttuynia Cordata Extract, Perilla Frutescens Leaf Extract, Ginkgo Biloba Leaf Extract, Panax Ginseng Root Extract, Chamaecyparis Obtusa Water, Cysteine, Camellia Japonica Seed Oil, Olea Europaea (Olive) Fruit Oil

PURPOSE

Purpose: Anti dandruff

WARNINGS

Warnings: For external use only 1. Avoid using on the following area. Scalp and skin affected by eczema. 2. Be cautious in the following case. Anyone who suffered from allergies (dermatitis due to rash, flare, itchiness, and lacquer) by drug or cosmetic 3. Consult with the doctor or pharmacist after discontinuing the use in case of symptoms, such as rash, flare and itchiness, caused by the usage of the drug. 4. General caution 1) Avoid contact with eyes. In case of contact with eyes, promptly rinse with water. In case the symptom is severe, receive treatment by an ophthalmologist. 2) Use the drug only for external use and not for internal use. 5. Caution on storage 1) Avoid direct sunlight and store in a cool place if possible. 2) Do not put in other container to maintain its quality and prevent misuse. 3) Avoid the location exposed to open flame and keep out of reach of children.

KEEP OUT OF REACH OF CHILDREN

INDICATIONS & USAGE

Indications & Usage: ① Prevention efficacy of dandruff by keeping the hygiene of the scalp ② May have the efficacy on hair loss prevention as well as hair thickness improvement ③ Hypo-allergenic on scalp with 23 types of natural components ④ Containing beer yeast extracts with abundant vitamin and protein ⑤ Enhancement of luster and elasticity by nourishing the scalp and hair

DOSAGE & ADMINISTRATION

Dosage & Administration: ① Wet the scalp and hair with warm water sufficiently. ② Put the adequate amount on the palm and make enough foam. ③ Gently massage the scalp with the fingertip, and the hair with the palm for 1~3 minutes. ④ Rinse the hair after 3 minutes.